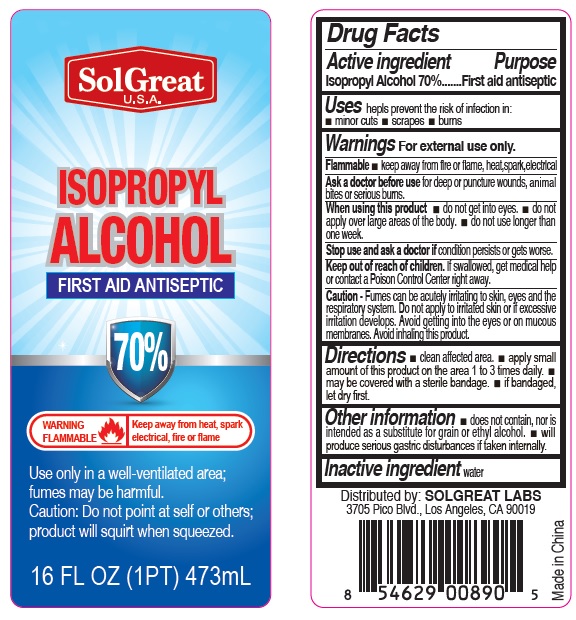 DRUG LABEL: SolGreat Isopropyl Alcohol
NDC: 73913-007 | Form: LIQUID
Manufacturer: PANATURAL USA, INC.
Category: otc | Type: HUMAN OTC DRUG LABEL
Date: 20200423

ACTIVE INGREDIENTS: ISOPROPYL ALCOHOL 70 mL/100 mL
INACTIVE INGREDIENTS: WATER

SolGreat Isopropyl Alcohol

Active lngredient

Isopropyl alcohol

Purpose

First aid antiseptic

Uses

helps prevent the risk of infection in:

- minor cuts
- scrapes
- burns

Warnings

For external use only

Flammable

- keep away from fire or flame, heat, spark, electrical

Ask a doctor before use for deep or puncture wounds, animal bites or serious burns.

When using this product

- do not get into eyes.
- do not apply over large areas of the body.
- do not use longer than one week.

Stop use and ask a doctor if condition persists or gets worse.

Caution – Fumes can be acutely irritating to skin, eyes and the respiratory system. Do not apply to irritated skin or if excessive irritation

develops. Avoid getting into the eyes or on mucous membranes. Avoid inhaling this product

Directions

- clean affected area.
- apply small amount of this product on the area 1 to 3 times daily.
- may be covered with a sterile bandage.
- if bandaged, let dry first.

Keep out of reach of children.

If swallowed, get medical help or contact a Poison Control Center right away.

Other information

- does not contain, nor is intended as a substitute for grain or ethyl alcohol.
- will produce serious gastric disturbances if taken internally

Inactive ingredient

water